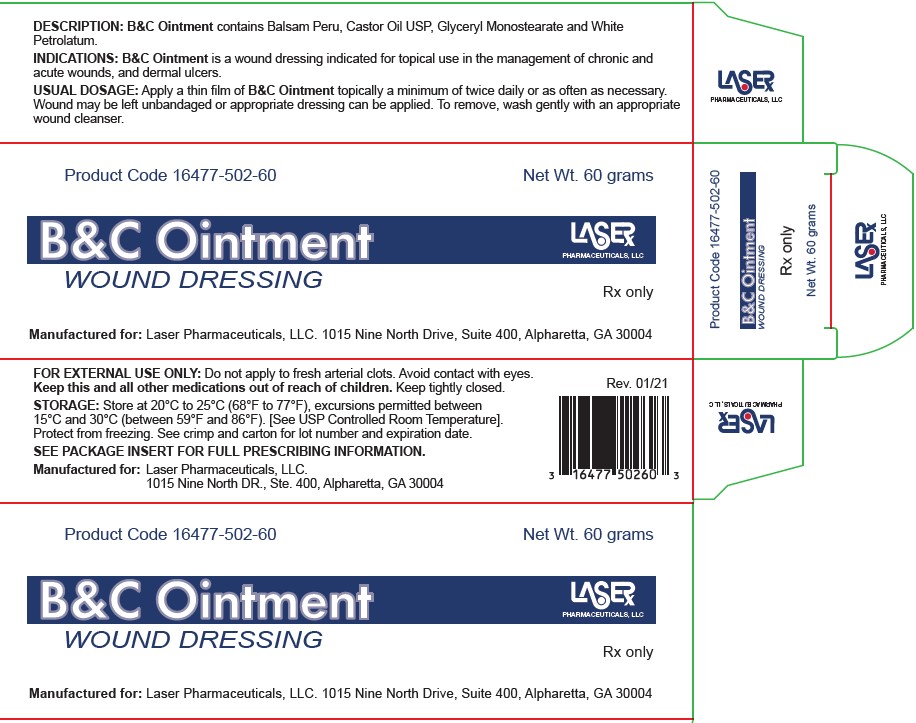 DRUG LABEL: B and C Ointment
NDC: 16477-502
Manufacturer: Laser Pharmaceuticals, LLC
Category: other | Type: MEDICAL DEVICE
Date: 20211026
INACTIVE INGREDIENTS: CASTOR OIL; BALSAM PERU; GLYCERYL MONOSTEARATE; PETROLATUM

B&C OINTMENT

B&C Ointment

WOUND DRESSING

Rx Only

DESCRIPTION

B&C OINTMENT contains Balsam Peru, Castor Oil USP, Glyceryl Monostearate and White Petrolatum.

ACTION

B&C OINTMENT helps to deodorize and protectively cover pressure wounds (ulcers). B&C OINTMENT provides a moist wound environment. The moisturizing properties of B&C OINTMENT may also help in the prevention of cracking around the edges of sores.

INDICATIONS

B&C OINTMENT is a wound dressing for topical use in the management of chronic and acute wounds, and dermal ulcers including: pressure ulcers (Stage I-IV), venous stasis ulcers, diabetic ulcers, first and second degree burns, surgical wounds, traumatic wounds, superficial wounds, ulcers resulting from arterial insufficiency and grafted wound/donor sites.

CONTRAINDICATIONS

B&C OINTMENT is contraindicated in persons who have shown hypersensitivity to Balsam Peru, Petrolatum or any of the other ingredients used in this ointment.

USES

B&C OINTMENT is easy to apply and quickly reduces odors frequently accompanying a decubitus ulcer. The wound may be left open or appropriate dressing applied. Please note that wounds generally heal poorly in the presence of hemoglobin or zinc deficiency.

WARNING

FOR EXTERNAL USE ONLY. Do not apply to fresh arterial clots. Avoid contact with eyes. Keep this and all other medications out of reach of children. Keep tightly closed. Use only as directed by a physician. When applied to a sensitive area, a temporary stinging may occur.

USUAL DOSAGE

Apply a thin film of B&C OINTMENT topically a minimum of twice daily or as often as necessary. Wound may be left unbandaged or appropriate dressing can be applied. To remove, wash gently with an appropriate wound cleanser.

HOW SUPPLIED

B&C OINTMENT is supplied as follows:

SIZE PRODUCT CODE

60 GRAM TUBE 16477-502-60

STORAGE

Store at 20°C to 25°C (68°F to 77°F), excursions permitted between 15°C and 30°C (between 59°F and 86°F). Brief exposure to temperatures up to 40°C (104°F) may be tolerated provided the mean kinetic temperature does not exceed 25°C (77°F); however, such exposure should be minimized. [See USP Controlled Room Temperature]. Protect from freezing. See crimp for lot number and expiration date.